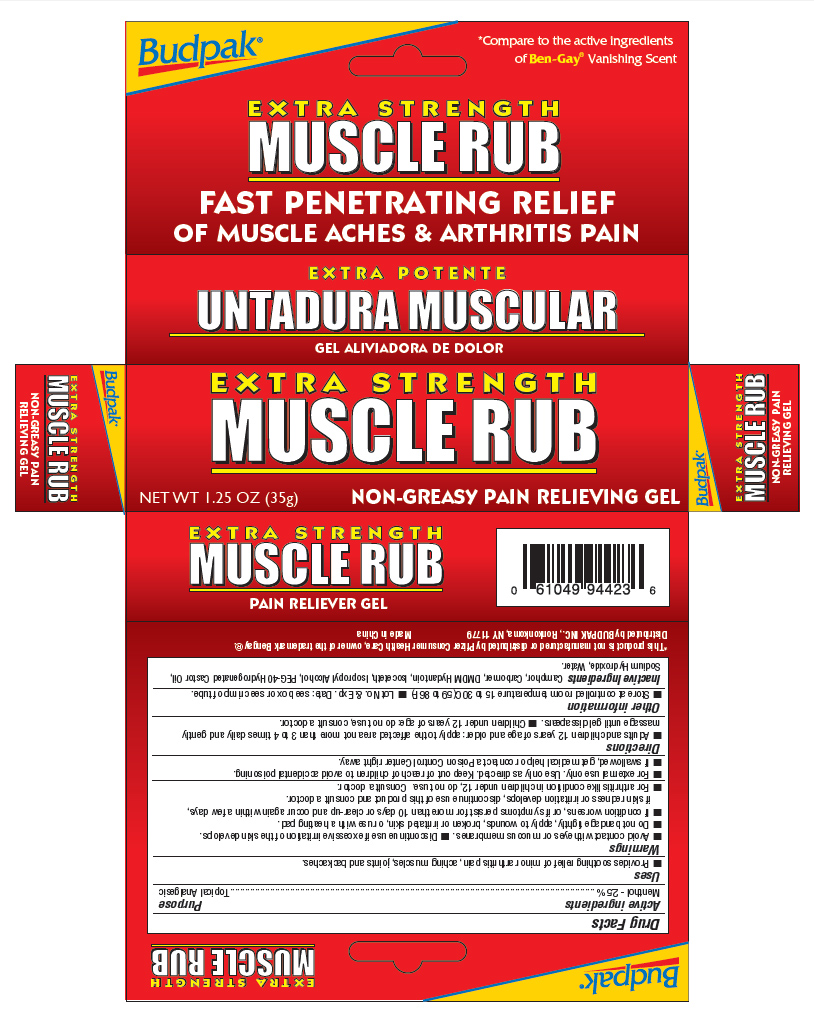 DRUG LABEL: Budpack
NDC: 27293-030 | Form: GEL
Manufacturer: Budpack Inc.
Category: otc | Type: HUMAN OTC DRUG LABEL
Date: 20120608

ACTIVE INGREDIENTS: MENTHOL 2.5 g/100 g
INACTIVE INGREDIENTS: CAMPHOR (SYNTHETIC); DMDM HYDANTOIN; ISOPROPYL ALCOHOL; POLYOXYL 40 HYDROGENATED CASTOR OIL; SODIUM HYDROXIDE; WATER

Drug Facts

Active Ingredients
Menthol 2.5%

Purpose
Topical Analgesic

INDICATIONS AND USAGE

Uses ▪ Provides soothing relief of minor arthritis pain, aching muscles, joints and backache.

Warnings

▪ Avoid contact with eyes or mucous membranes. ▪ Discontinue use if excessive irritation of the skin develops. ▪ Do not bandage tightly, apply to wounds, broken or irritated skin, or use with a heating pad. ▪ If condition worsens, or if symptoms persist for more than 10 days or clear-up and occur again within a few days, if skin redness or irritation develops, discontinue use of this product and consult a doctor. For arthritis like conditions in children under 12, do not use. Consult a doctor.

KEEP OUT OF REACH OF CHILDREN

▪For external use only.Use only as directed. Keep out of the reach of children to avoid accidental poisoning.
▪If swallowed, get medical help or contact a Poison Control Center right away

Directions

▪ Adults and children12 years of age and older: apply to affected area not more than 3-4 times daily and gently massage until gel disappears. ▪ Children under 12 years of age: do not use, consult a doctor

Other Information

▪Store at controlled room temperature 15 to 30C (59 to 86F) ▪ Lot No. Exp. Date: see box or see crimp of tube.

INACTIVE INGREDIENT

Inactive Ingredients Camphor, Carbomer, DMDM Hydantoin, Isoceteth, Isopropyl Alcohol,PEG-40 Hydrogenated Castor Oil, Sodium Hydroxide and Water

Package Label